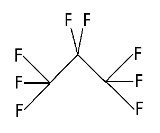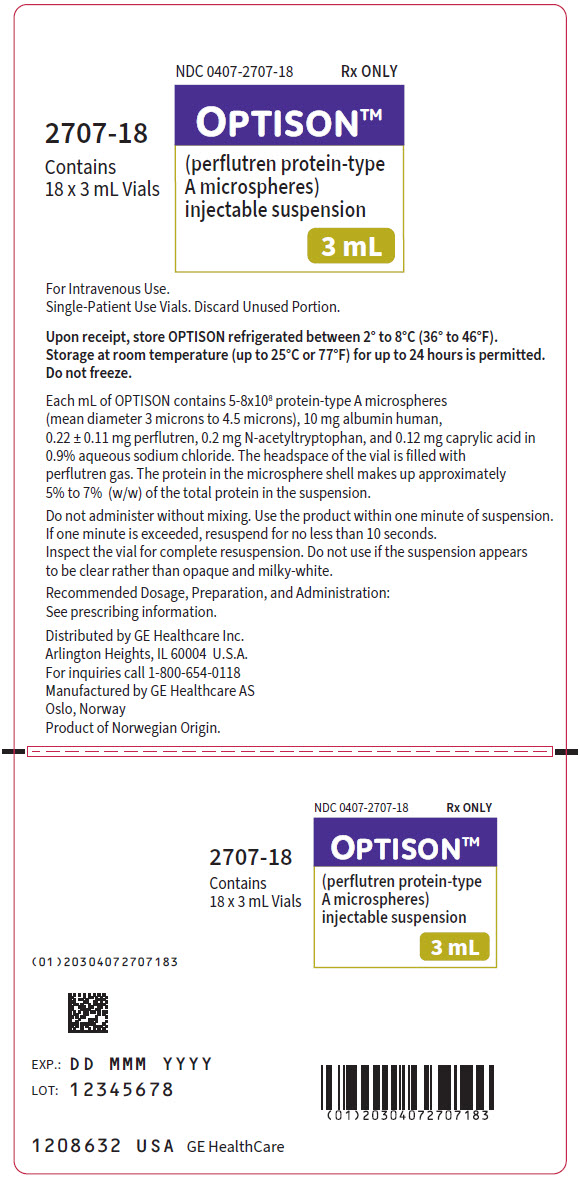 DRUG LABEL: Optison
NDC: 0407-2707 | Form: INJECTION, SOLUTION
Manufacturer: GE Healthcare Inc.
Category: prescription | Type: HUMAN PRESCRIPTION DRUG LABEL
Date: 20251217

ACTIVE INGREDIENTS: HUMAN ALBUMIN MICROSPHERES 10 mg/1 mL; PERFLUTREN 0.22 mg/1 mL
INACTIVE INGREDIENTS: N-ACETYL-DL-TRYPTOPHAN 0.2 mg/1 mL; CAPRYLIC ACID 0.12 mg/1 mL; SODIUM CHLORIDE

HIGHLIGHTS OF PRESCRIBING INFORMATION

These highlights do not include all the information needed to use OPTISON safely and effectively. See full prescribing information for OPTISON.
OPTISON (perflutren protein-type A microspheres) injectable suspension, for intravenous use
Initial U.S. Approval: 1997

WARNING: SERIOUS CARDIOPULMONARY REACTIONS

See full prescribing information for complete boxed warning.

Serious cardiopulmonary reactions, including fatalities, have occurred uncommonly during or following perflutren-containing microsphere administration. Most serious reactions occur within 30 minutes of administration (5.1).

- Assess all patients for the presence of any condition that precludes OPTISON administration (4).
- Always have resuscitation equipment and trained personnel readily available (5.1).

RECENT MAJOR CHANGES

Indications and Usage (1) | 5/2025
Dosage and Administration, Recommended Dosage (2.1) | 5/2025
Dosage and Administration, Preparation Instructions (2.2) | 5/2025
Dosage and Administration, Administration Instructions (2.3) | 5/2025
Warnings and Precautions, Transmissible Infectious Agents (5.5) - Removed | 5/2025

1 INDICATIONS AND USAGE

OPTISON is an ultrasound contrast agent indicated for use in adult and pediatric patients with suboptimal echocardiograms to opacify the left ventricle and to improve the delineation of the left ventricular endocardial borders (1).

2 DOSAGE AND ADMINISTRATION

- Adults
  - 0.5 mL intravenously at a rate not exceeding 1 mL/s.
  - If contrast enhancement is inadequate after the dose of 0.5 mL, additional doses of 0.5 mL may be repeated up to a total of 5 mL in a 10-minute period with a maximum total dose of 8.7 mL in any one patient study (2.1).
- Pediatric Patients
  - 28 kg or less: 0.2 mL diluted with 0.2 mL of 0.9% Sodium Chloride Injection.
  - 29 kg to 40 kg: 0.3 mL diluted with 0.3 mL of 0.9% Sodium Chloride Injection.
  - 41 kg or more: 0.4 mL diluted with 0.4 mL of 0.9% Sodium Chloride Injection.
  - Administer intravenously at a rate not exceeding 0.05 mL/s.
  - If contrast enhancement is inadequate after the initial dose, up to four additional doses of the same diluted volume may be repeated for further contrast enhancement as needed (2.1).
- Follow the OPTISON injection with a flush of 0.9% Sodium Chloride Injection or 5% Dextrose Injection (2.3).
- See full prescribing information for preparation instructions (2.2).

3 DOSAGE FORMS AND STRENGTHS

Injectable suspension: 5-8 ×10^8/mL protein-type A microspheres, 10 mg/mL albumin human, and 0.22 ± 0.11 mg/mL perflutren in 3 mL single-patient use vials (3)

4 CONTRAINDICATIONS

Known or suspected hypersensitivity to perflutren or albumin (4)

5 WARNINGS AND PRECAUTIONS

Hypersensitivity Reactions: Serious anaphylactic reactions have been observed. Always have cardiopulmonary resuscitation personnel and equipment readily available prior to OPTISON administration and monitor all patients for hypersensitivity reactions (5.2).

6 ADVERSE REACTIONS

Common adverse reactions (incidence ≥ 0.5%) were: headache, nausea and/or vomiting, warm sensation or flushing, dizziness, dysgeusia, chills or fever, flu-like symptoms, malaise/weakness/fatigue, chest pain, dyspnea, injection site discomfort, and erythema (6.1).

To report SUSPECTED ADVERSE REACTIONS, contact GE HealthCare at 1-800-654-0118 or FDA at 1-800-FDA-1088 or www.fda.gov/medwatch.

FULL PRESCRIBING INFORMATION

WARNING: SERIOUS CARDIOPULMONARY REACTIONS

Serious cardiopulmonary reactions, including fatalities, have occurred uncommonly during or following perflutren-containing microsphere administration. Most serious reactions occur within 30 minutes of administration [see Warnings and Precautions (5.1)].

- Assess all patients for the presence of any condition that precludes OPTISON administration [see Contraindications (4)].
- Always have resuscitation equipment and trained personnel readily available [see Warnings and Precautions (5.1)].

1 INDICATIONS AND USAGE

OPTISON is indicated for use in adult and pediatric patients with suboptimal echocardiograms to opacify the left ventricle and to improve the delineation of the left ventricular endocardial borders.

2 DOSAGE AND ADMINISTRATION

2.1 Recommended Dosage

Adults

- The recommended dose in adults is 0.5 mL administered intravenously at a rate not exceeding 1 mL/s [see Dosage and Administration (2.3)].
- If the contrast enhancement is inadequate after the dose of 0.5 mL, additional doses of 0.5 mL may be repeated for further contrast enhancement as needed.
- The maximum total dose is 5 mL in any 10-minute period.
- The maximum total dose is 8.7 mL in any one patient study.

Pediatric Patients

- The recommended dose by body weight in pediatric patients is shown in Table 1.
- Administer by intravenous injection at a rate not exceeding 0.05 mL/s [see Dosage and Administration (2.3)].
- If the contrast enhancement is inadequate after the initial dose, up to four additional doses of the same diluted volume may be repeated for further contrast enhancement as needed.
- OPTISON must be diluted with 0.9% Sodium Chloride Injection to form a 1:1 dilution for pediatric administration [see Dosage and Administration (2.2)].
  Table 1. Recommended Dose of OPTISON by Body Weight in Pediatric Patients
  Body Weight | Dose
  28 kg or less | 0.2 mL of OPTISON diluted with 0.2 mL of 0.9% Sodium Chloride Injection
  29 kg to 40 kg | 0.3 mL of OPTISON diluted with 0.3 mL of 0.9% Sodium Chloride Injection
  41 kg or more | 0.4 mL of OPTISON diluted with 0.4 mL of 0.9% Sodium Chloride Injection

2.2 Preparation Instructions

General

- Visually inspect the OPTISON vial. Do not use if the container has been damaged, the protective seal and/or rubber cap have been entered, or the upper white layer is absent (may indicate the microspheres have been damaged and may result in poor or no echo contrast).
- Invert the vial and gently rotate to resuspend the microspheres. This process will allow the product to come to room temperature (20°C to 25°C or 68°F to 77°F) before use.
- Inspect the vial for complete resuspension. Do not use if the suspension appears to be clear rather than opaque and milky-white.
- Vent the OPTISON vial with a sterile vent spike or with a sterile 18-gauge needle before withdrawing the OPTISON suspension into the injection syringe.
- Do not inject air into the vial.
- Use the product within one minute of suspension. If one minute is exceeded, resuspend by inverting and gently rotating the syringe for no less than 10 seconds. Failure to adequately resuspend OPTISON may cause inadequate delivery of the microspheres and may result in inadequate contrast.

Dilution for Pediatric Administration

- Invert the OPTISON vial and gently rotate to resuspend the microspheres.
- Draw equal volumes of OPTISON and 0.9% Sodium Chloride Injection into the same syringe to form a 1:1 dilution.
- Mix gently by holding the syringe horizontally between the palms and rolling it gently back and forth for at least 10 seconds.
- If not used within 10 minutes after dilution, discard the diluted product.

2.3 Administration Instructions

- OPTISON is for intravenous use only and must not be administered by intra-arterial injection [see Warnings and Precautions (5.3)].
- Inspect visually for foreign particulate matter and discoloration prior to administration, whenever suspension and container permit. Do not inject if the suspension is not opaque and milky-white, or foreign particulate matter is present.
- For adults, inject through a 20-gauge or larger angiocatheter into a peripheral vein at a rate not exceeding 1 mL/s as a faster rate may reduce performance of the OPTISON microspheres.
- For pediatric patients, inject through a 24-gauge or larger angiocatheter into a peripheral vein at a rate not exceeding 0.05 mL/s as a faster rate may reduce performance of the OPTISON microspheres.
- Suggested methods of administration include: a short extension tubing, heparin lock, or intravenous line, all with a 3-way stopcock.
- Do not aspirate blood back into the OPTISON-containing syringe before administration; this may promote the formation of a blood clot within the syringe.
- For short extension tubing or heparin lock, fill one syringe with 10 mL of 0.9% Sodium Chloride Injection for adults or 5 mL of 0.9% Sodium Chloride Injection for pediatric patients and flush the line for patency before and after the injection of OPTISON.
- For a continuous intravenous line, open an intravenous line with 0.9% Sodium Chloride Injection or 5% Dextrose Injection to maintain vascular patency. Flush the line in its entirety immediately after injection of OPTISON.
- Each vial is for single-patient use. Discard unused portion.

3 DOSAGE FORMS AND STRENGTHS

Injectable suspension: 5-8×10^8/mL protein-type A microspheres, 10 mg/mL albumin human, and 0.22 ± 0.11 mg/mL perflutren as a clear liquid lower layer, a white liquid upper layer, and a headspace filled with perflutren gas in 3 mL single-patient use vial; after resuspension, OPTISON is a sterile, homogeneous, opaque, and milky-white injectable suspension.

4 CONTRAINDICATIONS

OPTISON is contraindicated in patients with known or suspected hypersensitivity to perflutren or albumin [see Warnings and Precautions (5.2)].

5 WARNINGS AND PRECAUTIONS

5.1 Serious Cardiopulmonary Reactions

Serious cardiopulmonary reactions including fatalities have occurred uncommonly during or shortly following perflutren-containing microsphere administration, typically within 30 minutes of administration. The risk for these reactions may be increased among patients with unstable cardiopulmonary conditions (acute myocardial infarction, acute coronary artery syndromes, worsening or unstable congestive heart failure, or serious ventricular arrhythmias).

The reported reactions to perflutren-containing microspheres include: fatal cardiac or respiratory arrest, shock, syncope, symptomatic arrhythmias (atrial fibrillation, tachycardia, bradycardia, supraventricular tachycardia, ventricular fibrillation, ventricular tachycardia), hypertension, hypotension, dyspnea, hypoxia, chest pain, respiratory distress, stridor, wheezing, loss of consciousness and convulsions [see Adverse Reactions (6.2)].

Always have cardiopulmonary resuscitation personnel and equipment readily available prior to OPTISON administration and monitor all patients for acute reactions.

5.2 Hypersensitivity Reactions

Serious anaphylactic reactions have been observed during or shortly following perflutren-containing microsphere administration including: shock, hypersensitivity, bronchospasm, throat tightness, angioedema, edema (pharyngeal, palatal, mouth, peripheral, localized), swelling (face, eye, lip, tongue upper airway), facial hypoesthesia, rash, urticaria, pruritus, flushing, and erythema have occurred in patients with no prior exposure to perflutren-containing microsphere products. Always have cardiopulmonary resuscitation personnel and equipment readily available prior to OPTISON administration and monitor all patients for hypersensitivity reactions [see Adverse Reactions (6.2)].

5.3 Systemic Embolization

When administering OPTISON to patients with a cardiac shunt, microspheres can bypass filtering of the lung and enter the arterial circulation. Assess patients with shunts for embolic phenomena following OPTISON administration. OPTISON is only for intravenous administration; do not administer OPTISON by intra-arterial injection.

5.4 Ventricular Arrhythmia Related to High Mechanical Index

High ultrasound mechanical index values may cause microsphere rupture and lead to ventricular arrhythmias. Additionally, end-systolic triggering with high mechanical indices has been reported to cause ventricular arrhythmias. OPTISON is not recommended for use at mechanical indices greater than 0.8.

6 ADVERSE REACTIONS

The following serious adverse reactions are described elsewhere in the labeling:

- Serious Cardiopulmonary Reactions [see Warnings and Precautions (5.1)]
- Hypersensitivity Reactions [see Warnings and Precautions (5.2)]

6.1 Clinical Trials Experience

Because clinical trials are conducted under widely varying conditions, adverse reaction rates observed in the clinical trials of a drug cannot be directly compared to rates in the clinical trials of another drug and may not reflect the rates observed in practice.

Adverse Reactions in Adults

The safety of OPTISON was evaluated in 279 adult patients in clinical studies. These patients were 69% male, 31% female, 71% White, 19% Black or African American, 9% Hispanic or Latino, and 1% other racial or ethnic groups. Adverse reactions reported in ≥ 0.5% of patients who received OPTISON by intravenous injection are given in Table 2.

Table 2. Adverse Reactions Reported in ≥ 0.5% of the Adult Patients who Received OPTISON in Controlled Clinical Studies
Adverse Reaction | OPTISON n=279 %
Body as a Whole
Headache | 5.4
Warm Sensation/Flushing | 3.6
Chills/fever | 1.4
Flu-like Symptoms | 1.1
Malaise/Weakness/Fatigue | 1.1
Cardiovascular System
Dizziness | 2.5
Chest Pain | 1.1
Digestive System
Nausea and/or Vomiting | 4.3
Respiratory System
Dyspnea | 1.1
Skin & Appendages
Injection Site Discomfort | 1.1
Erythema | 0.7
Special Senses
Dysgeusia | 1.8

Adverse reactions reported in < 0.5% of patients who received OPTISON included:

Body as a Whole: induration, discoloration at the injection site
Cardiovascular system: premature ventricular contractions, palpitations
Digestive system: dry mouth
Immune system disorders: hypersensitivity
Musculoskeletal and connective tissue disorders: back pain, arthralgia, body or muscle aches
Nervous system: tremor, paresthesia, irritableness
Respiratory system: oxygen saturation decline due to coughing, wheezing
Skin and appendages: urticaria, rash, pruritus
Special Senses: tinnitus, visual blurring, photophobia, burning sensation in the eyes

Adverse Reactions in Pediatric Patients

Overall, the safety profile observed in pediatric patients from the clinical study was consistent with the safety profile in adult patients [see Clinical Studies (14.2)].

6.2 Postmarketing Experience

Adverse Reactions from Observational Studies

In a prospective, post-marketing safety surveillance study of OPTISON used in routine clinical practice, a total of 1,039 patients received OPTISON. These patients had an average age of 59.9 years (min, max: 20, 97) and were 62% male, 38% female, 83% White, 14% Black or African American, 2% Asian, and 1.5% other racial or ethnic groups. Overall, 17% of patients reported at least one adverse event. No deaths or serious adverse reactions were reported in this study.

Adverse Reactions from Postmarking Spontaneous Reports

The following adverse reactions have been identified during the postmarketing use of OPTISON or other perflutren-containing microspheres. Because these reactions are reported voluntarily from a population of uncertain size, it is not always possible to reliably estimate their frequency or establish a causal relationship to drug exposure.

Cardiopulmonary

Fatal cardiac or respiratory arrest, shock, syncope, symptomatic arrhythmias (atrial fibrillation, tachycardia, bradycardia, supraventricular tachycardia, ventricular fibrillation, ventricular tachycardia), hypertension, hypotension, dyspnea, hypoxia, chest pain, respiratory distress or decreased oxygenation, stridor, wheezing.

Immune System

Anaphylaxis with manifestations that may include death, shock, bronchospasm, throat tightness, angioedema, edema (pharyngeal, palatal, mouth, peripheral, localized), swelling (face, eye, lip, tongue, upper airway), facial hypoesthesia, rash, urticaria, pruritus, flushing, erythema.

Neurologic

Loss of consciousness, convulsion

8 USE IN SPECIFIC POPULATIONS

8.1 Pregnancy

Risk Summary

There are no data with OPTISON use in pregnant women to inform any drug-associated risks. No adverse developmental outcomes were observed in animal reproduction studies with intravenous administration of OPTISON to pregnant rats and rabbits during organogenesis at doses up to at least 5 and 10 times the recommended human dose based on body surface area (see Data).

In the U.S. general population, the estimated background risk of major birth defects and miscarriage in clinically recognized pregnancies is 2% to 4% and 15% to 20%, respectively.

Data

Animal Data

OPTISON was administered intravenously to rats at doses of 0.25, 5 and 10 mL/kg/day (approximately 0.2, 5, and 10 times the recommended maximum human dose of 8.7 mL, respectively, based on body surface area) and to rabbits at 0.25, 2.5, and 5 mL/kg/day (approximately 0.5, 5, and 10 times the recommended maximum human dose, respectively, based on body surface area) during organogenesis. No significant findings attributable solely to a direct effect on the fetus were detected in the studies.

8.2 Lactation

There are no data on the presence of perflutren protein-type A microspheres in human milk, the effects on the breastfed infant, or the effects on milk production. The developmental and health benefits of breastfeeding should be considered along with the mother's clinical need for OPTISON and any potential adverse effects on the breastfed infant from OPTISON or from the underlying maternal condition.

8.4 Pediatric Use

The safety and effectiveness of OPTISON to opacify the left ventricle and improve the delineation of the left ventricular endocardial borders have been established in pediatric patients with suboptimal echocardiograms. Use of OPTISON in pediatric patients is supported by evidence from adequate and well-controlled studies in adults and additional efficacy and safety data from a clinical study in 37 pediatric patients aged 9 to 17 years old [see Adverse Reactions (6.1) and Clinical Studies (14.1, 14.2)].

8.5 Geriatric Use

Of the total number of subjects in a clinical study of OPTISON, 35% were 65 and over, while 14% were 75 and over. No overall differences in safety or effectiveness were observed between these subjects and younger subjects, and other reported clinical experience has not identified differences in responses between the elderly and younger patients, but greater sensitivity of some older individuals cannot be ruled out.

11 DESCRIPTION

OPTISON (perflutren protein-type A microspheres) injectable suspension is an ultrasound contrast agent for intravenous use.

Perflutren is chemically characterized as 1,1,1,2,2,3,3,3-perflutren with a molecular weight of 188, an empirical formula of C3F8, and the following structural formula:

Each mL contains 5-8×10^8 protein-type A microspheres, 10 mg albumin human, 0.22 ± 0.11 mg perflutren, and the following inactive ingredients: 0.2 mg N-acetyltryptophan and 0.12 mg caprylic acid in 0.9% aqueous sodium chloride. The headspace of the vial is filled with perflutren gas. The pH is adjusted to 6.4 to 7.4. The protein in the microsphere shell makes up approximately 5% to 7% (w/w) of the total protein in the suspension. The microsphere particle size parameters are listed in Table 3.

OPTISON is supplied as a clear liquid lower layer, a white liquid upper layer, and a headspace filled with perflutren gas, and after resuspension, OPTISION is a sterile, homogeneous, opaque, and milky-white suspension.

Table 3. Microsphere Size Distribution
Parameter
Mean diameter (range) | 3 to 4.5 µm
Percent less than 10 µm | 95%
Maximum diameter | 32 µm

12 CLINICAL PHARMACOLOGY

12.1 Mechanism of Action

The OPTISON microspheres create an echogenic contrast effect in the blood. The acoustic impedance of the OPTISON microspheres is much lower than that of the blood. Therefore, impinging ultrasound waves are scattered and reflected at the microsphere-blood interface and ultimately may be visualized in the ultrasound image. At the frequencies used in adult echocardiography (2 MHz to 5 MHz), the microspheres resonate which further increases the extent of ultrasound scattering and reflection.

12.2 Pharmacodynamics

Contrast Enhancement Duration in Adults

The median duration of OPTISON contrast enhancement for each of the four doses of OPTISON, 0.2 (40% of recommended dose), 0.5, 3, and 5 mL, were approximately one, two, four, and five minutes, respectively [see Clinical Studies (14.1)].

Pulmonary Hemodynamic Effects

The effect of OPTISON on pulmonary hemodynamics was studied in a prospective, open-label study of 30 patients scheduled for pulmonary artery catheterization, including 19 with an elevated baseline pulmonary arterial systolic pressure (PASP) (>35 mmHg) and 11 with a normal PASP (≤35 mmHg). Systemic hemodynamic parameters and ECGs were also evaluated. No clinically important pulmonary hemodynamic, systemic hemodynamic, or ECG changes were observed.

12.3 Pharmacokinetics

After injection of OPTISON, diffusion of the perflutren gas out of the microspheres is limited by the low partition coefficient of the gas in blood that contributes to the persistence of the microspheres.

The pharmacokinetics of the intact microspheres of OPTISON in humans are unknown.

Distribution

The binding of perflutren to plasma proteins and its partitioning into blood cells are unknown. However, perflutren protein binding is expected to be minimal due to the low partition coefficient of the gas in blood.

Elimination

Following intravenous injection, perflutren is cleared with a pulmonary elimination half-life of 1.3 ± 0.69 minutes (mean ± SD).

Metabolism

Perflutren is a stable gas that is not metabolized. The human albumin component of the microsphere is expected to be handled by the normal metabolic routes.

Excretion

Perflutren is eliminated through the lungs within 10 minutes. The mean ± SD recovery was 96% ± 23%. The perflutren concentration in expired air peaked approximately 30 to 40 seconds after administration.

13 NONCLINICAL TOXICOLOGY

13.1 Carcinogenesis, Mutagenesis, Impairment of Fertility

Carcinogenesis

Animal studies were not carried out to determine the carcinogenic potential of OPTISON.

Mutagenesis

The result of the following genotoxicity studies with OPTISON were negative: 1) Salmonella/Escherichia coli reverse mutation assay, 2) in vitro mammalian chromosome aberration assay using Chinese hamster ovary cells (CHO) with and without metabolic activation, 3) CHO/HGPRT forward mutation assay, and 4) in vivo mammalian micronucleus assay.

14 CLINICAL STUDIES

14.1 Echocardiography in Adults

The effectiveness of OPTISON was evaluated in two identical multicenter, controlled, dose escalation studies in 203 adult patients (Study A: n=101, Study B: n=102) with sub-optimal non-contrast echocardiography defined as having at least two out of six segments of the left ventricular endocardial border inadequately delineated in the apical 4-chamber view. These patients were 79% male, 21% female, 64% White, 25% Black or African American, 10% Hispanic or Latino, and 1% other race or ethnic group. The patients had a mean age of 61 years (range: 21 years to 83 years), a mean weight of 196 lbs. (range: 117 lbs. to 342 lbs.), a mean height of 68 inches (range: 47 inches to 78 inches), and a mean body surface area of 2 m^2 (range: 1.4 m^2 to 2.6 m^2). Approximately 23% of the patients had chronic pulmonary disease, and 17% had congestive and dilated cardiomyopathy with left ventricular ejection fractions (LVEFs) between 20% and 40% (by previous echocardiography). Patients with a LVEF of less than 20% or with New York Heart Association Class IV heart failure were not included in the studies.

After non-contrast imaging, OPTISON was administered in increasing increments as four doses (0.2, 0.5, 3, and 5 mL) with at least 10 minutes between each dose. Ultrasound settings were optimized for the baseline (non-contrast) apical 4-chamber view and remained unchanged for the contrast imaging. Static echocardiographic images and video-tape segments were interpreted by a reader who was blinded to the patient's clinical history and to the dose of OPTISON. Left ventricular endocardial border delineation and left ventricular opacification were assessed before and after OPTISON administration by the measurement of visualized endocardial border length and ventricular opacification.

In comparison to non-contrast ultrasound, OPTISON significantly increased the length of endocardial border that could be visualized both at end-systole and end-diastole (see Table 4). In these patients there was a trend towards less visualization in women. OPTISON increased left ventricular opacification (peak intensity) in the mid-chamber and apical views (see Table 5). The imaging effects of OPTISON on endocardial border delineation and left ventricular opacification were similar at doses between 0.5 mL and 5 mL and were also similar among patients with or without pulmonary disease and dilated cardiomyopathy.

Table 4. Left Ventricular Endocardial Border Length Visualized Before and After OPTISON in Adults [The differences in the number of enrolled patients and evaluated patients at each dose reflect exclusions based on withdrawal from the trial, or those with technically inadequate or missing images.] , [An intent-to-treat analysis, with non-favorable values imputed for missing patients, provided qualitatively similar results.]
Study | OPTISON dose | Length at End-Systole (cm) |  | Length at End-Diastole (cm)
 | OPTISON dose | n | mean ± S.D. | n | mean ± S.D.
Study A (n=101) | 0 mL (baseline) | 87 | 7.7 ± 3.0 | 86 | 9.3 ± 3.4
Study A (n=101) | 0.5 mL | 86 | 12.0 ± 4.9 | 91 | 15.8 ± 5.1
Study B (n=102) | 0 mL (baseline) | 89 | 8.1 ± 3.4 | 89 | 9.6 ± 3.7
Study B (n=102) | 0.5 mL | 95 | 12.4 ± 4.9 | 97 | 16.4 ± 4.6

Table 5. Intensity of Left Ventricular Opacification [Intensity measured by videodensitometry in arbitrary gray scale units (0-255).] Before and After OPTISON in Adults [The differences in the number of enrolled patients and evaluated patients at each dose reflect exclusions based on withdrawal from the trial, or those with technically inadequate or missing images.] , [An intent-to-treat analysis, with non-favorable values imputed for missing patients, provided qualitatively similar results.]
Study | OPTISON dose | Mid-Chamber |  |  |  | Apex
 | OPTISON dose | Intensity at End-Diastole |  | Intensity at End-Systole |  | Intensity at End-Diastole |  | Intensity at End-Systole
 | OPTISON dose | n | mean ± S.D. | n | mean ± S.D. | n | mean ± S.D. | n | mean ± S.D.
Study A (n=101) | 0 mL (baseline) | 91 | 39.5 ± 16.9 | 91 | 40.0 ± 18.1 | 91 | 46.7 ± 19.7 | 91 | 46.9 ± 20.1
Study A (n=101) | 0.5 mL | 91 | 57.3 ± 26.8 | 90 | 57.4 ± 26.7 | 91 | 67.0 ± 30.1 | 90 | 64.1 ± 30.2
Study B (n=102) | 0 mL (baseline) | 95 | 40.4 ± 17.4 | 95 | 40.9 ± 17.5 | 95 | 43.7 ± 19.9 | 95 | 45.0 ± 19.6
Study B (n=102) | 0.5 mL | 97 | 53.3 ± 20.7 | 96 | 53.6 ± 21.0 | 97 | 64.4 ± 25.3 | 96 | 61.6 ± 26.7

14.2 Echocardiography in Pediatric Patients

The effectiveness of OPTISON was evaluated in a multicenter open-label clinical trial (NCT03740997) of 37 pediatric patients aged 9 to 17 years who were clinically indicated for transthoracic echocardiography and had suboptimal non-contrast echocardiography, defined as at least two contiguous segments in any view that could not be visualized.

These patients were 62% male, 38% female, 70% White, 8% Black or African American, 3% Asian, 3% American Indian or Alaska Native, 5% multiple races, 8% unknown race, and 3% race not reported. Ethnicity distribution was 49% Hispanic or Latino, 47% not Hispanic or Latino, and 3% not reported.

After non-contrast echocardiography, two increasing doses of OPTISON (dose level 1 and 2) based on body weight were administered with at least 10 minutes between doses. Contrast and non-contrast images for each patient were evaluated by three independent readers who were blinded to clinical information. Readers assessed visualization of 12 segments of the left ventricular wall in standard apical 4- and 2-chamber views on a 4-point Endocardial Border Delineation scale (0 to 3, indicating no, poor, fair, and good/optimal visualization). Segments scored 2 or 3 were considered visualized. The mean number of visualized segments of left ventricular wall under non-contrast echocardiography, echocardiography following OPTISON at dose level 2 (0.2 mL, 0.3 mL, or 0.4 mL, depending on body weight), and the difference (OPTISON at dose level 2 minus non-contrast) for the 37 patients in the full analysis set are shown in Table 6.

Table 6. Mean Number of Left Ventricular Wall Segments Visualized by Reader in Pediatric Patients (n=37 patients) [The full analysis set population consists of all 37 enrolled patients who had echocardiographic images collected both before and after OPTISON administration, irrespective of the quality of the OPTISON images. The number of segments visualized was based on the Endocardial Border Delineation score (segments rated as "2 = fair visualization" or "3 = good/optimal visualization") and ranged from 0 to 12.]
Reader | Non-Contrast Mean (SD) | OPTISON Dose Level 2 [Dose level 2 was 0.2 mL, 0.3 mL, or 0.4 mL, depending on body weight] Mean (SD) | Difference Between OPTISON Dose Level 2 & Non-Contrast Mean (95% CI) [CI=Confidence Interval]
Reader 1 | 3.3 (3.4) | 9.2 (4.3) | 5.9 (4.4, 7.5)
Reader 2 | 2.8 (2.8) | 9.0 (4.7) | 6.2 (4.4, 8.1)
Reader 3 | 4.6 (5.0) | 9.3 (4.1) | 4.6 (2.6, 6.7)

16 HOW SUPPLIED/STORAGE AND HANDLING

How Supplied

OPTISON (perflutren protein-type A microspheres) injectable suspension is supplied at concentrations of 5-8×10^8/mL protein-type A microspheres, 10 mg/mL albumin human, and 0.22 ± 0.11 mg/mL perflutren as a clear liquid lower layer, a white liquid upper layer, and a headspace filled with perflutren gas in 3 mL single-patient use vials. After resuspension, OPTISON is a sterile, homogeneous, opaque, and milky-white injectable suspension.

- Five (5) – 3 mL vials per carton
- Eighteen (18) – 3 mL vials per carton

NDC 0407-2707-03
NDC 0407-2707-18

Storage and Handling

Upon receipt, store OPTISON refrigerated between 2°C to 8°C (36°F to 46°F). Storage at room temperature (up to 25°C or 77°F) for up to 24 hours is permitted. Do not freeze.

17 PATIENT COUNSELING INFORMATION

Hypersensitivity Reactions

Advise patients to inform their healthcare provider if they develop any symptoms of hypersensitivity after OPTISON administration including rash, wheezing, or shortness of breath [see Warnings and Precautions (5.2)].

Distributed by
GE Healthcare Inc.
Arlington Heights, IL 60004

OPTISON™ is a trademark of GE HealthCare or one of its subsidiaries.
GE is a trademark of General Electric Company used under trademark license.

© 2025 GE HealthCare

PRINCIPAL DISPLAY PANEL - 3 mL Vial Carton Label

NDC 0407-2707-18
Rx ONLY

OPTISON™
(perflutren protein-type
A microspheres)
injectable suspension
3 mL

2707-18
Contains
18 x 3 mL Vials

(01)20304072707183

EXP.: DD MMM YYYY
LOT: 12345678

1208632 USA GE HealthCare